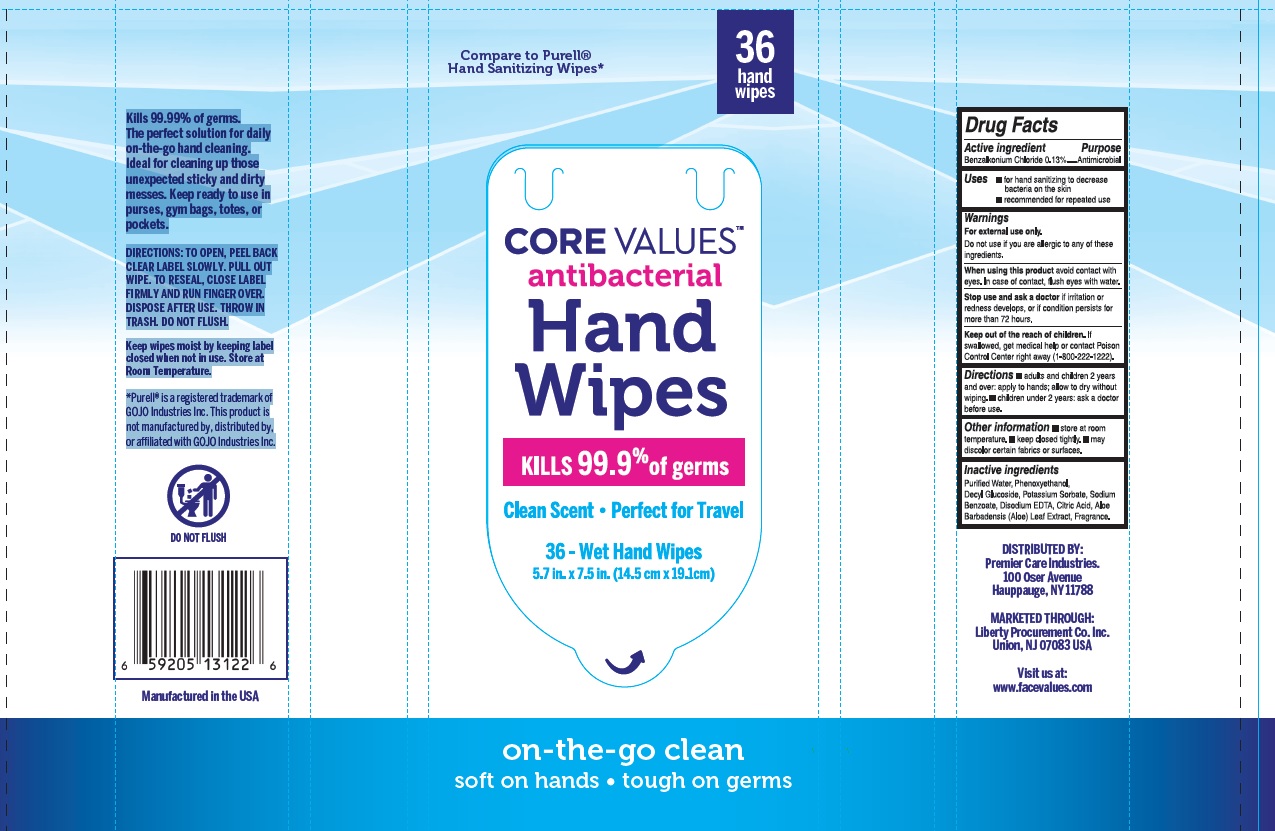 DRUG LABEL: Hand Wipes
NDC: 63940-036 | Form: SWAB
Manufacturer: Harmon Stores Inc.
Category: otc | Type: HUMAN OTC DRUG LABEL
Date: 20241216

ACTIVE INGREDIENTS: BENZALKONIUM CHLORIDE 0.13 g/100 g
INACTIVE INGREDIENTS: WATER; PHENOXYETHANOL; DECYL GLUCOSIDE; POTASSIUM SORBATE; SODIUM BENZOATE; EDETATE DISODIUM ANHYDROUS; CITRIC ACID MONOHYDRATE; ALOE VERA LEAF

Drug Facts

Active ingredient

Benzalkonium chloride.........0.13%

Purpose

Antimicrobial

Uses

- For hand sanitizing to decrease bacteria on the skin
- Recommended for repeated use

Warnings

For external use only

Do not use if you are allergic to any of these ingredients

When using this product

avoid contact with eyes. In case of eye contact, flush eyes with water.

Stop use and ask a doctor

If irritation or redness develops, or if condition persists for more than 72 hours.

Keep out of reach of children

If swallowed, get medical help or contact a Poison Control Center right away (1-800-222-1222)

Directions

- adults and childrens 2 years and over: apply to hands, allow to dry without wiping
- children under 2 years: ask a doctor before use

Other information

- Store at room temperature
- keep closed tightly
- may discolor certain fabrics or surfaces

Inactive ingredients

Purified Water, Phenoxyethanol, Decyl Glucoside, Potassium Sorbate, Sodium Benzoate, Disodium EDTA, Citric Acid, Aloe Barbadensis (Aloe) Leaf Extract, Fragrance.

Principal Display Panel

NDC: 63940-036-36

Compare to Purell® Hand Sanitizing Wipes

36 hand wipes

CORE VALUESTMantibacterial

Hand Wipes

KILLS 99.9% of germs

Clean Scent

Perfect for Travel

36 - Wet Hand Wipes

5.7 in. x 7.5 in. (14.5cm x 19.1cm)